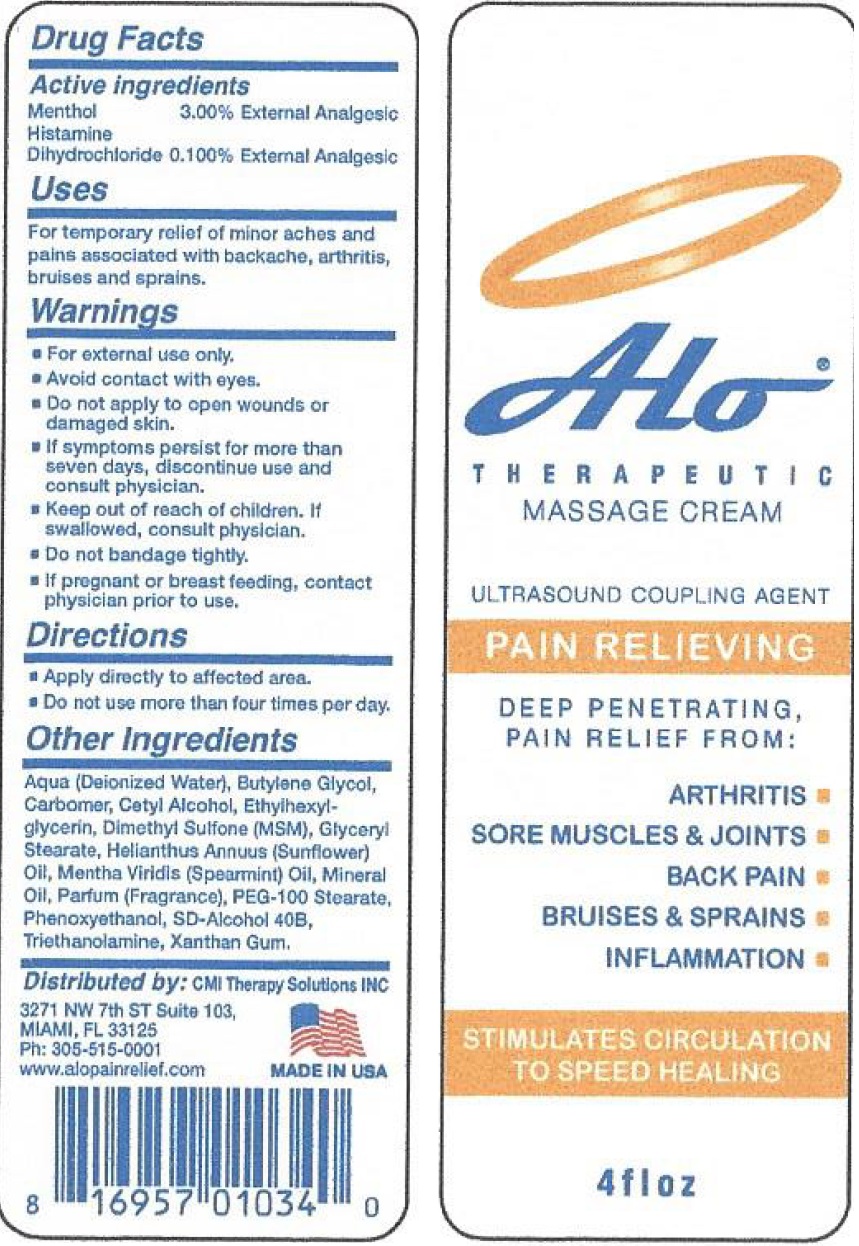 DRUG LABEL: Alo Therapeutic Massage
NDC: 71061-763 | Form: CREAM
Manufacturer: CMI Therapy Solutions
Category: otc | Type: HUMAN OTC DRUG LABEL
Date: 20231110

ACTIVE INGREDIENTS: MENTHOL 30 mg/1 mL; HISTAMINE DIHYDROCHLORIDE 1 mg/1 mL
INACTIVE INGREDIENTS: WATER; BUTYLENE GLYCOL; CARBOXYPOLYMETHYLENE; CETYL ALCOHOL; ETHYLHEXYLGLYCERIN; DIMETHYL SULFONE; GLYCERYL MONOSTEARATE; SUNFLOWER OIL; SPEARMINT OIL; MINERAL OIL; PEG-100 STEARATE; PHENOXYETHANOL; TROLAMINE; XANTHAN GUM

Alo Therapeutic Massage Cream

Active ingredients

Menthol 3.00%

Histamine Dihydrochloride 0.100%

PURPOSE

External Analgesic

Uses

For temporary relief of minor aches and pains associated with backache, arthritis, bruises and sprains.

Warnings

- For external use only.
- Avoid contact with eyes.

Do not apply

- to open wounds or damaged skin.
- If symptoms persist for more than seven days, discontinue use and consult physician.

Keep out of reach of children.

If swallowed, consult physician.

Do not bandage tightly.

If pregnant or breast feeding,

contact physician prior to use.

Directions

- Apply directly to affected area.
- Do not use more than four times per day.

Other Ingredients

Aqua (deionized Water), Butylene Glycol, Carbomer, Cetyl Alcohol, Ethylhexylglycerin, Dimethyl Sulfone (MSM), Glyceryl Stearate, Helianthus Annuus (Sunflower) Oil, Mentha Viridis (Spearmint) Oil, Mineral Oil, Parfum (Fragrance), PEG-100 Stearate, Phenoxyethanol, SD-Alcohol 40B, Triethanolamine, Xanthan Gum.